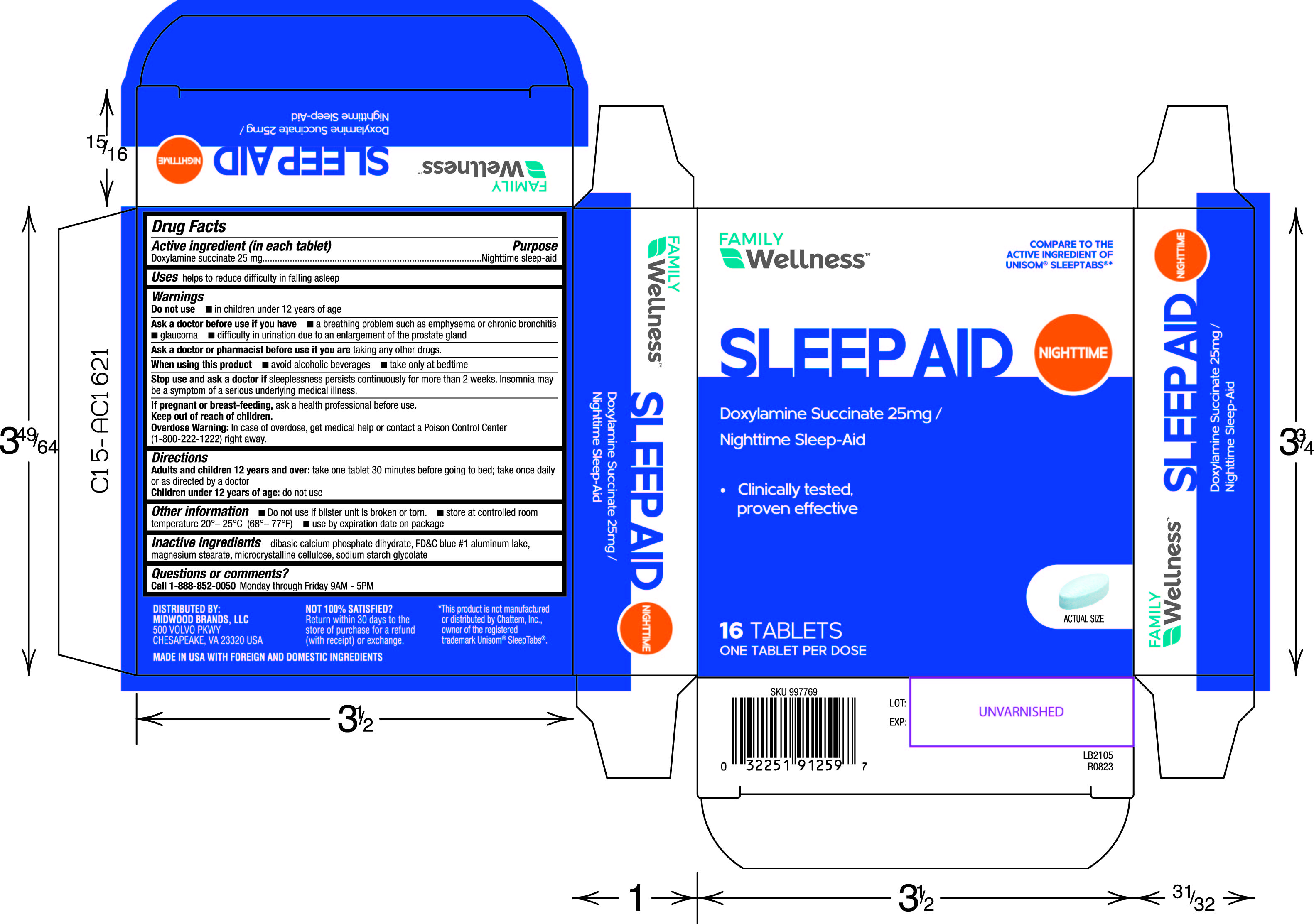 DRUG LABEL: Nighttime Sleep Aid
NDC: 55319-439 | Form: TABLET
Manufacturer: Family Dollar Stores, Inc
Category: otc | Type: HUMAN OTC DRUG LABEL
Date: 20230725

ACTIVE INGREDIENTS: DOXYLAMINE SUCCINATE 25 mg/1 1
INACTIVE INGREDIENTS: DIBASIC CALCIUM PHOSPHATE DIHYDRATE; FD&C BLUE NO. 1 ALUMINUM LAKE; MAGNESIUM STEARATE; MICROCRYSTALLINE CELLULOSE; SODIUM STARCH GLYCOLATE TYPE A POTATO

439- Nighttime Sleep Aid

Active ingredient(s)

Doxylamine succinate 25 mg

Purpose

Nighttime sleep-aid

Use(s)

helps to reduce difficulty in falling asleep

Warnings

Do not use

- in children under 12 years of age

Ask a doctor before use if

- a breathing problem such as emphysema or chronic bronchitis
- glaucoma
- difficulty in urination due to an enlargement of the prostate gland

Ask a doctor or pharmacist before use if

you are taking any other drugs.

When using this product

- avoid alcoholic beverages
- take only at bedtime

Stop use and ask a doctor if

sleeplessness persists continuously for more than 2 weeks. Insomnia may be a symptom of
a serious underlying medical illness.

If pregnant or breastfeeding,

ask a health professional before use.

Keep out of reach of children

Overdose Warning: In case of overdose, get medical help or contact a Poison Control Center (1-800-222-1222) right away.

Directions

Adults and children 12 years and over: take one tablet 30 minutes before going to bed; take once daily or as directed by a
doctor
Children under 12 years of age: do not use

Other information

- Do not use if blister unit is broken or torn
- store at controlled room temperature 20°– 25°C (68°– 77°F)
- use by expiration date on package

Inactive ingredients

dibasic calcium phosphate dihydrate, FD&C blue #1 aluminum lake, magnesium stearate,
microcrystalline cellulose, sodium starch glycolate

Questions/Comments

Call 1-888-952-0050 Monday through Friday 9AM - 5PM

Principal Display Panel

Sleep Aid